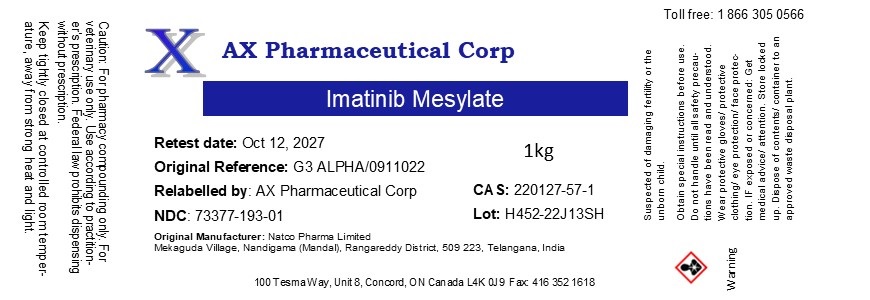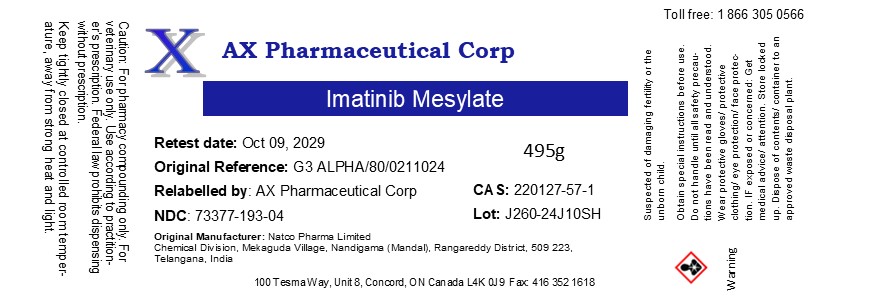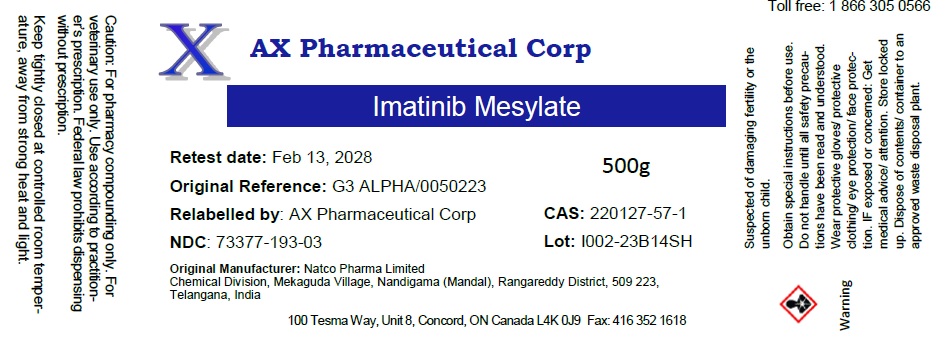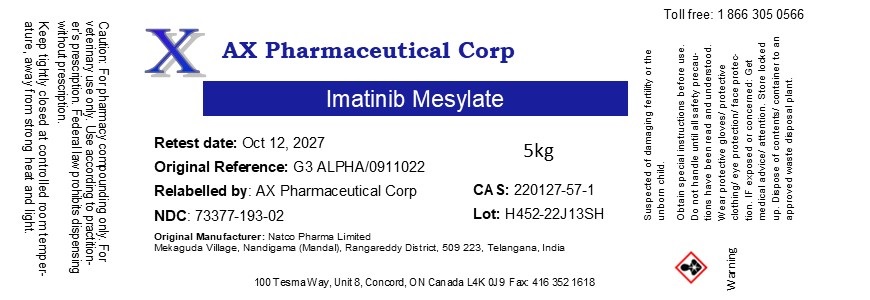 DRUG LABEL: Imatinib Mesylate
NDC: 73377-193 | Form: POWDER
Manufacturer: AX Pharmaceutical Corp
Category: other | Type: BULK INGREDIENT - ANIMAL DRUG
Date: 20250115

ACTIVE INGREDIENTS: IMATINIB MESYLATE 1 g/1 g

Imatinib Mesylate